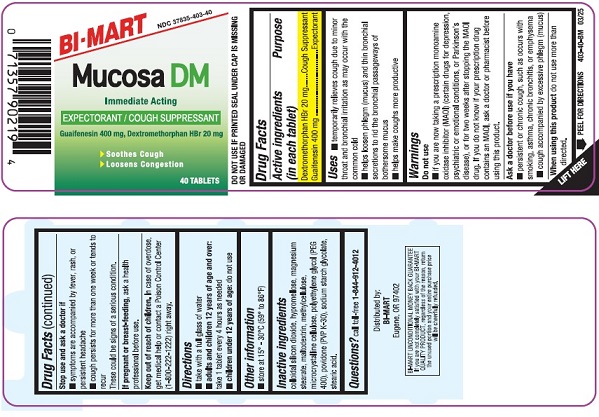 DRUG LABEL: MUCUS RELIEF DM
NDC: 37835-403 | Form: TABLET
Manufacturer: Bi-Mart
Category: otc | Type: HUMAN OTC DRUG LABEL
Date: 20250601

ACTIVE INGREDIENTS: DEXTROMETHORPHAN HYDROBROMIDE 20 mg/1 1; GUAIFENESIN 400 mg/1 1
INACTIVE INGREDIENTS: SILICON DIOXIDE; HYPROMELLOSE, UNSPECIFIED; METHYLCELLULOSE, UNSPECIFIED; MAGNESIUM STEARATE; MALTODEXTRIN; MICROCRYSTALLINE CELLULOSE; POLYETHYLENE GLYCOL 400; POVIDONE K30; SODIUM STARCH GLYCOLATE TYPE A; STEARIC ACID

MUCUS RELIEF DM

Active ingredient (in each tablet)

Dextromethorphan HBr 20 mg
Guaifenesin 400 mg

Purpose

Cough Suppressant

Expectorant

Uses

- temporarily relieves cough due to minor throat and bronchial irritation as may occur with the common cold
- helps loosen phlegm (mucus) and thin bronchial secretions to rid the bronchial passageways of bothersome mucus
- help make coughs more productive

Warnings

Do not use

- if you are now taking a prescription monoamine oxidase inhibitor (MAOI) (certain drugs for depression, psychiatric or emotional conditions, or Parkinson’s disease), or for 2 weeks after stopping the MAOI drug. If you do not know if your prescription drug contains a MAOI, ask a doctor or pharmacist before taking this product.

Ask a doctor before use if you have

- persistent or chronic cough such as occurs with smoking, asthma, chronic bronchitis, or emphysema
- cough accompanied by excessive phlegm (mucus)

When using this product

do not use more than directed.

Stop use and ask a doctor if

- symptoms are accompanied by fever, rash, or persistent headache
- cough persists for more than one week or tends to recur

These could be signs of a serious condition.

If pregnant or breast-feeding,

ask a health professional before use.

Keep out of reach of children,

In case of overdose, get medical help or contact a Poison Control Center (1-800-222-1222) right away.

Directions

- take with a full glass of water
- adults and children 12 years of age and over:take 1 tablet every 4 hours as needed
- Children under 12 years of age: do not use

Other information

- store at 15° - 30°C (59° to 86°F)

Inactive ingredients

colloidal silicon dioxide, hypromellose, magnesium stearate, maltodextrin, microcrystalline cellulose, polyethylene glycol (PEG 400), povidone (PVP K-30), sodium starch glycolate, stearic acid.

Questions?

call toll-free 1-844-912-4012